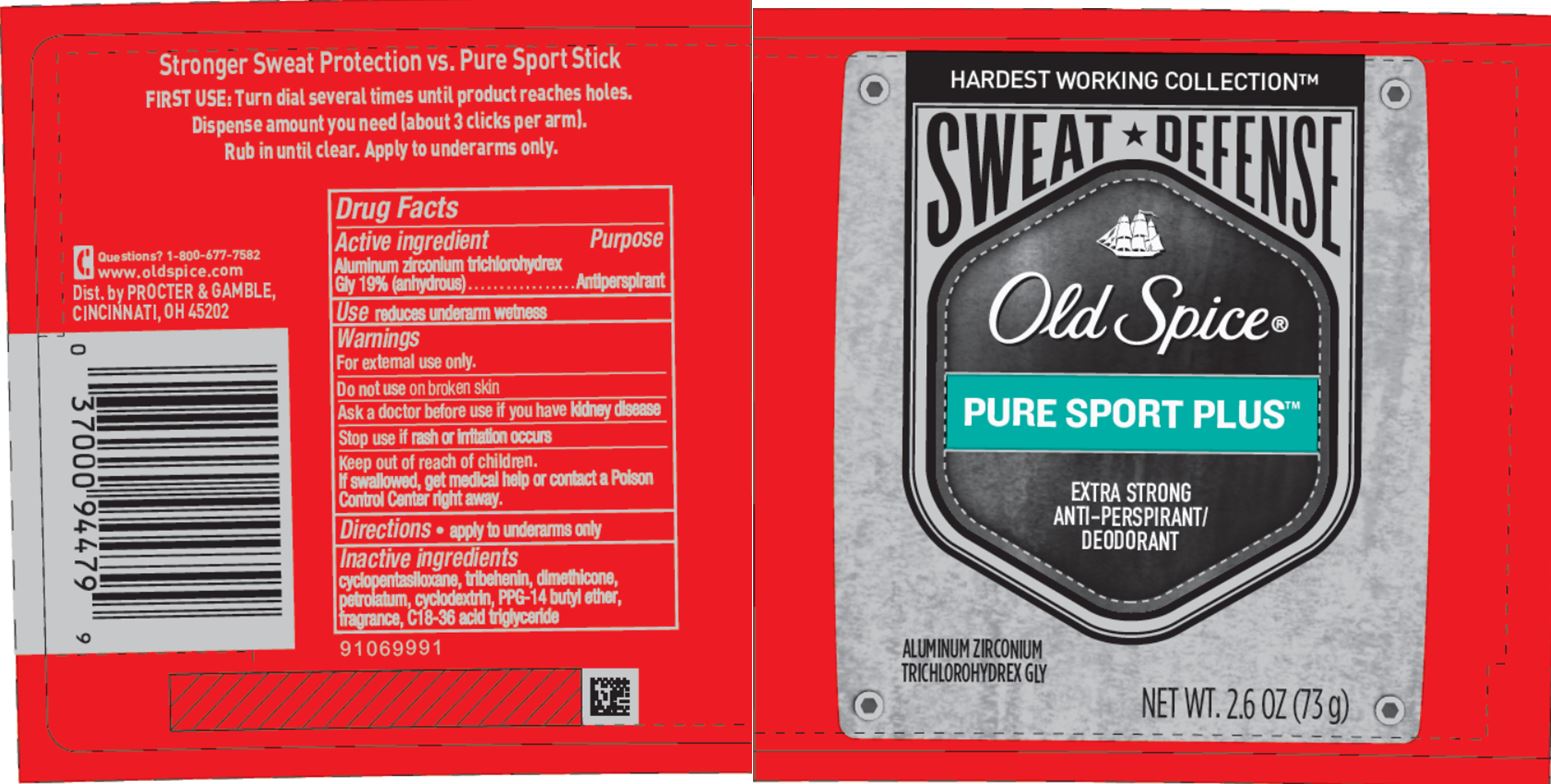 DRUG LABEL: Old Spice Sweat Defense Pure Sport Plus
NDC: 69423-055 | Form: STICK
Manufacturer: The Procter & Gamble Manufacturing Company
Category: otc | Type: HUMAN OTC DRUG LABEL
Date: 20251215

ACTIVE INGREDIENTS: ALUMINUM ZIRCONIUM TRICHLOROHYDREX GLY 19 g/100 g
INACTIVE INGREDIENTS: C18-36 ACID TRIGLYCERIDE; CYCLOMETHICONE 5; DIMETHICONE; PETROLATUM; TRIBEHENIN; PPG-14 BUTYL ETHER

Old Spice® Sweat Defense Pure Sport Plus™

Drug Facts

Active ingredient

Aluminum zirconium trichlorohydrex Gly 19% (anhydrous)

Purpose

Antiperspirant

Use

reduces underarm wetness

Warnings

For external use only.

Do not use on broken skin

Ask a doctor before use if you have kidney disease

Stop use if rash or irritation occurs

Keep out of reach of children.

If swallowed, get medical help or contact a Poison Control Center right away.

Directions

- apply to underarms only

Inactive ingredients

cyclopentasiloxane, tribehenin, dimethicone, petrolatum, cyclodextrin, PPG-14 butyl ether, fragrance, C18-36 acid triglyceride

Questions?

1-800-677-7582
www.oldspice.com

Dist. by PROCTER & GAMBLE,
CINCINNATI, OH 45202.

PRINCIPAL DISPLAY PANEL - 73 g Cylinder Label

HARDEST WORKING COLLECTION™

SWEAT DEFENSE

Old Spice®

PURE SPORT PLUS™

EXTRA STRONG
ANTI-PERSPIRANT/
DEODORANT

ALUMINUM ZIRCONIUM
TRICHLOROHYDREX GLY

NET WT. 2.6 OZ (73 g)